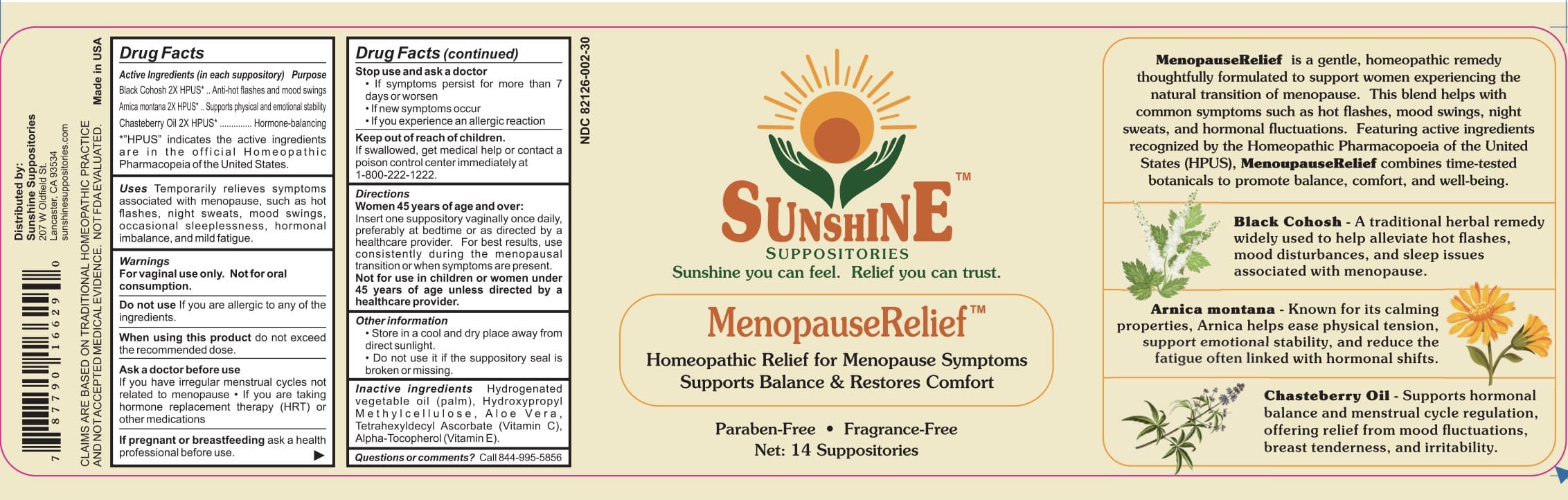 DRUG LABEL: Sunshine MenopauseRelief
NDC: 82126-002 | Form: SUPPOSITORY
Manufacturer: Apcco Labs, Inc
Category: homeopathic | Type: HUMAN OTC DRUG LABEL
Date: 20250618

ACTIVE INGREDIENTS: ARNICA MONTANA 2 [hp_X]/1 mg; BLACK COHOSH 2 [hp_X]/1 mg; CHASTE TREE FRUIT OIL 2 [hp_X]/1 mg
INACTIVE INGREDIENTS: HYDROGENATED PALM OIL; .ALPHA.-TOCOPHEROL ACETATE, DL-; HYPROMELLOSE 2910 (15 MPA.S); ALOE VERA LEAF; ASCORBYL TETRAISOPALMITATE

Apcco Labs, MenopauseRelief

ACTIVE INGREDIENTS:

Black Cohosh 2X HPUS* ... Anti-hot flashes and mood swings

Arnica montana 2X HPUS*......Supports physical and emotional stability

Chasteberry Oil 2X HPUS*|..... Hormone-balancing

*"HPUS" indicates the active ingredients are in the official Homeopathic

Pharmacopeia of the United States.

PURPOSE:

Anti-hot flashes and mood swings

Supports physical and emotional stability

Hormone-balancing

INDICATIONS:

Temporarily relieves symptoms associated with menopause, such as hot flashes, night sweats,

mood swings, occasional sleeplessness, hormonal imbalance, and mild fatigue.

WARNINGS:

For vaginal use only. Not for oral consumption.

Do not use If you are allergic to any of the ingredients.

When using this product do not exceed the recommended dose.

Ask a doctor before use

If you have irregular menstrual cycles not related to menopause • If you are taking hormone replacement therapy (HRT) or other medications

Stop use and ask a doctor

If symptoms persist for more than 7 days or worsen
If new symptoms occur
If you experience an allergic reaction

If pregnant or breast feeding, ask a health professional before use.

KEEP OUT OF REACH OF CHILDREN:

If swallowed, get medical help or contact a poison control center immediately at 1-800-222-1222.

DIRECTIONS:

Women 45 years of age and over:

Insert one suppository vaginally once daily, preferably at bedtime or as directed by a healthcare provider. For best results, use consistently during the menopausal transition or when symptoms are present.

Not for use in children or women under 45 years of age unless directed by a healthcare provider.

INACTIVE INGREDIENTS:

Hydrogenated

Hydroxypropyl

Methylcellulose,

Aloe Vera.

Tetrahexyldecyl Ascorbate (Vitamin C),

Alpha-Tocopherol (Vitamin E).

OTHER INFORMATION:

Store in a cool and dry place away from direct sunlight.
Do not use it if the suppository seal is broken or missing.

QUESTIONS:

Call 844-995-5856